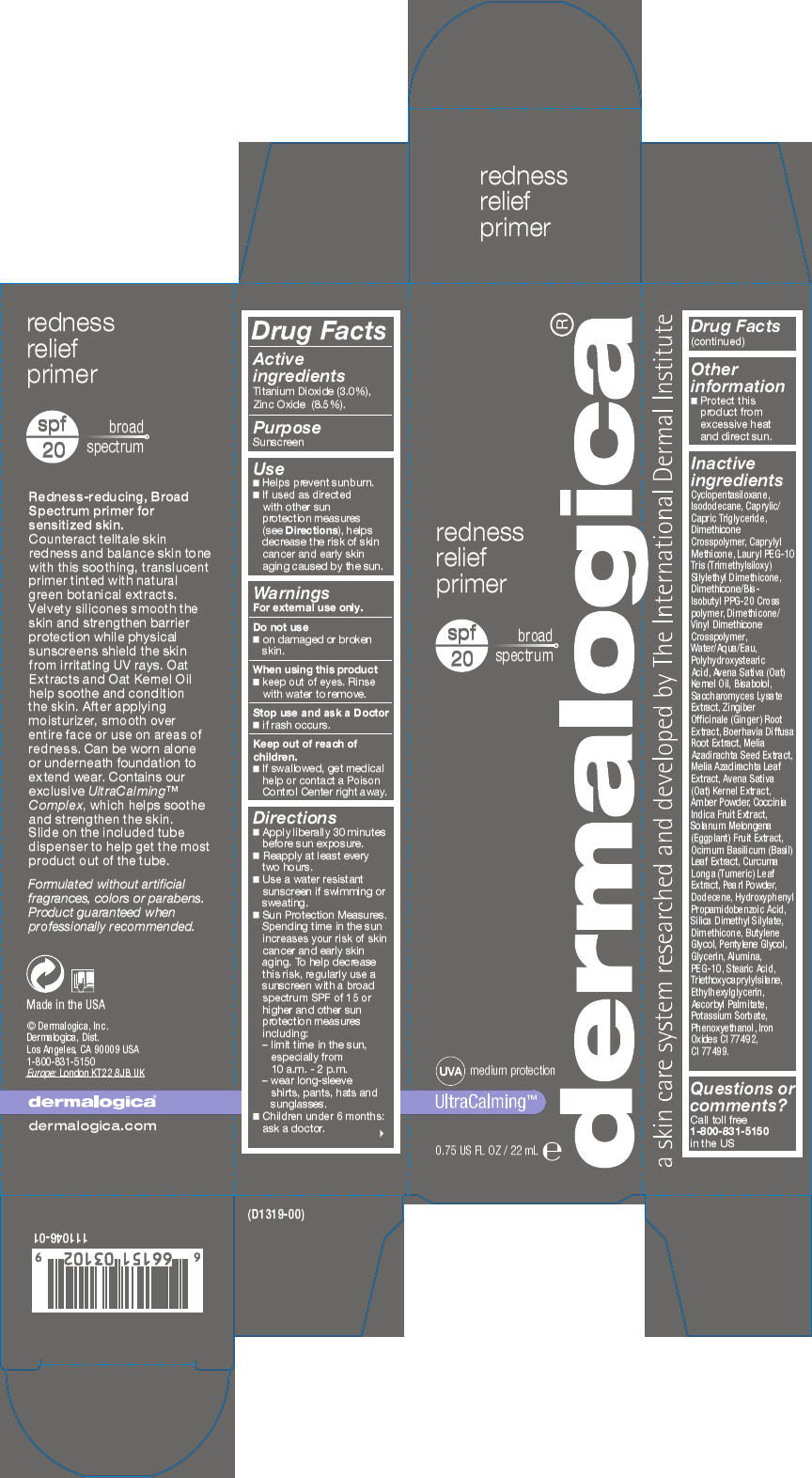 DRUG LABEL: Redness Relief Primer 
NDC: 68479-009 | Form: LOTION
Manufacturer: Dermalogica, Inc.
Category: otc | Type: HUMAN OTC DRUG LABEL
Date: 20151119

ACTIVE INGREDIENTS: Titanium Dioxide 30 mg/1 mL; Zinc Oxide 85 mg/1 mL
INACTIVE INGREDIENTS: Cyclomethicone 5; Isododecane; Medium-Chain Triglycerides; Caprylyl Trisiloxane; Dimethicone/Bis-Isobutyl PPG-20 Crosspolymer; Dimethicone/Vinyl Dimethicone Crosspolymer (Soft Particle); Water; Polyhydroxystearic Acid (2300 MW); Oat Kernel Oil; Levomenol; Saccharomyces Lysate; Ginger; Boerhavia Diffusa Root; Azadirachta Indica Seed; Azadirachta Indica Leaf; Oat; Amber; Coccinia Grandis Fruit; Eggplant; Basil; Curcuma Longa Leaf; Pearl (Hyriopsis Cumingii); Dodecene; Hydroxyphenyl Propamidobenzoic Acid; Silica Dimethyl Silylate; Dimethicone; Butylene Glycol; Pentylene Glycol; Glycerin; Aluminum Oxide; POLYETHYLENE GLYCOL 500; Stearic Acid; Triethoxycaprylylsilane; Ethylhexylglycerin; Ascorbyl Palmitate; Potassium Sorbate; Phenoxyethanol; Ferric Oxide Yellow; Ferrosoferric Oxide

Redness Relief Primer
SPF20

Drug Facts

Active ingredients

Titanium Dioxide (3.0%),
Zinc Oxide (8.5%).

Purpose

Sunscreen

Use

- Helps prevent sunburn.
- If used as directed with other sun protection measures (see Directions), helps decrease the risk of skin cancer and early skin aging caused by the sun.

Warnings

For external use only.

Do not use

- on damaged or broken skin.

When using this product

- keep out of eyes. Rinse with water to remove.

Stop use and ask a Doctor

- if rash occurs.

Keep out of reach of children.

- If swallowed, get medical help or contact a Poison Control Center right away.

Directions

- Apply liberally 30 minutes before sun exposure.
- Reapply at least every two hours.
- Use a water resistant sunscreen if swimming or sweating.
- Sun Protection Measures. Spending time in the sun increases your risk of skin cancer and early skin aging. To help decrease this risk, regularly use a sunscreen with a broad spectrum SPF of 15 or higher and other sun protection measures including:
  - limit time in the sun, especially from 10 a.m. - 2 p.m.
  - wear long-sleeve shirts, pants, hats and sunglasses.
- Children under 6 months: ask a doctor.

Other information

- Protect this product from excessive heat and direct sun.

Inactive ingredients

Cyclopentasiloxane, Isododecane, Caprylic/Capric Triglyceride, Dimethicone Crosspolymer, Caprylyl Methicone, Lauryl PEG-10 Tris (Trimethylsiloxy) Silylethyl Dimethicone, Dimethicone/Bis-Isobutyl PPG-20 Cross polymer, Dimethicone/Vinyl Dimethicone Crosspolymer, Water/Aqua/Eau, Polyhydroxystearic Acid, Avena Sativa (Oat) Kernel Oil, Bisabolol, Saccharomyces Lysate Extract, Zingiber Officinale (Ginger) Root Extract, Boerhavia Diffusa Root Extract, Melia Azadirachta Seed Extract, Melia Azadirachta Leaf Extract, Avena Sativa (Oat) Kernel Extract, Amber Powder, Coccinia Indica Fruit Extract, Solanum Melongena (Eggplant) Fruit Extract, Ocimum Basilicum (Basil) Leaf Extract, Curcuma Longa (Tumeric) Leaf Extract, Pearl Powder, Dodecene, Hydroxyphenyl Propamidobenzoic Acid, Silica Dimethyl Silylate, Dimethicone, Butylene Glycol, Pentylene Glycol, Glycerin, Alumina, PEG-10, Stearic Acid, Triethoxycaprylylsilane, Ethylhexylglycerin, Ascorbyl Palmitate, Potassium Sorbate, Phenoxyethanol, Iron Oxides CI 77492, CI 77499.

Questions or comments?

Call toll free 1-800-831-5150 in the US

PRINCIPAL DISPLAY PANEL - 22 mL Tube Carton

redness
relief
primer

spf
20
broad
spectrum

UVA medium protection

UltraCalming™

0.75 US FL OZ / 22 mL e

dermalogica®